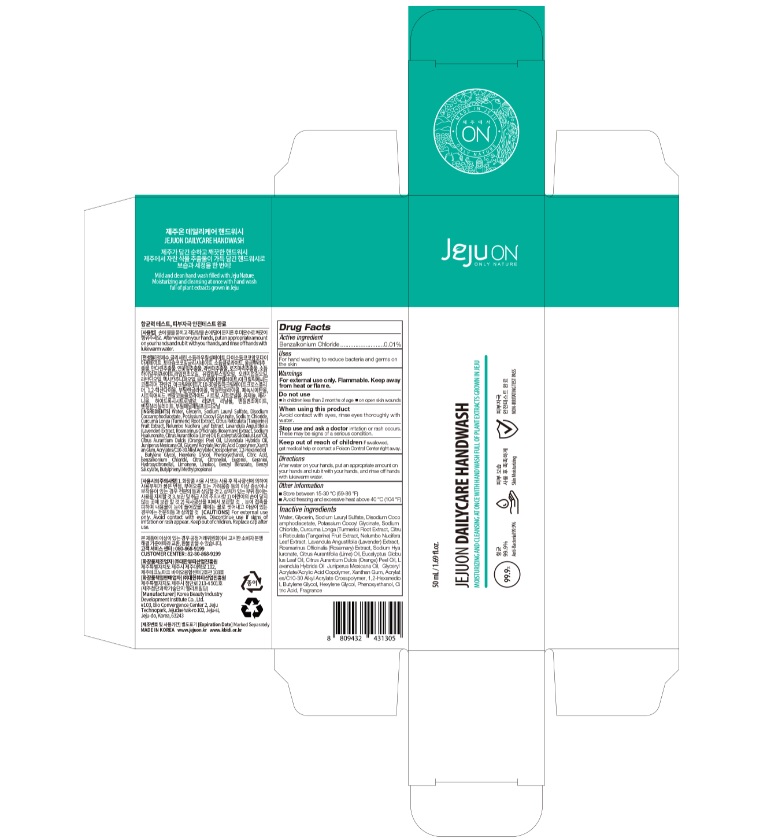 DRUG LABEL: JEJUON DailyCare Handwash
NDC: 76744-150 | Form: LIQUID
Manufacturer: Korea Beauty Industry Development Institute Co.,Ltd.
Category: otc | Type: HUMAN OTC DRUG LABEL
Date: 20200508

ACTIVE INGREDIENTS: BENZALKONIUM CHLORIDE 0.5 g/50 mL
INACTIVE INGREDIENTS: GLYCERIN; SODIUM LAURYL SULFATE; LAVANDULA ANGUSTIFOLIA FLOWERING TOP; LIME OIL; TURMERIC; HYALURONATE SODIUM; JUNIPERUS DEPPEANA WOOD OIL; CARBOMER INTERPOLYMER TYPE A (ALLYL SUCROSE CROSSLINKED); PHENOXYETHANOL; CITRIC ACID MONOHYDRATE; TANGERINE; NELUMBO NUCIFERA LEAF; ROSEMARY; ORANGE OIL; XANTHAN GUM; 1,2-HEXANEDIOL; HEXYLENE GLYCOL; SODIUM CHLORIDE; WATER; DISODIUM COCOAMPHODIACETATE; POTASSIUM COCOYL GLYCINATE; EUCALYPTUS OIL; LAVANDIN OIL; BUTYLENE GLYCOL

JEJUON DailyCare Handwash : Tube < Box : 76744-150-02